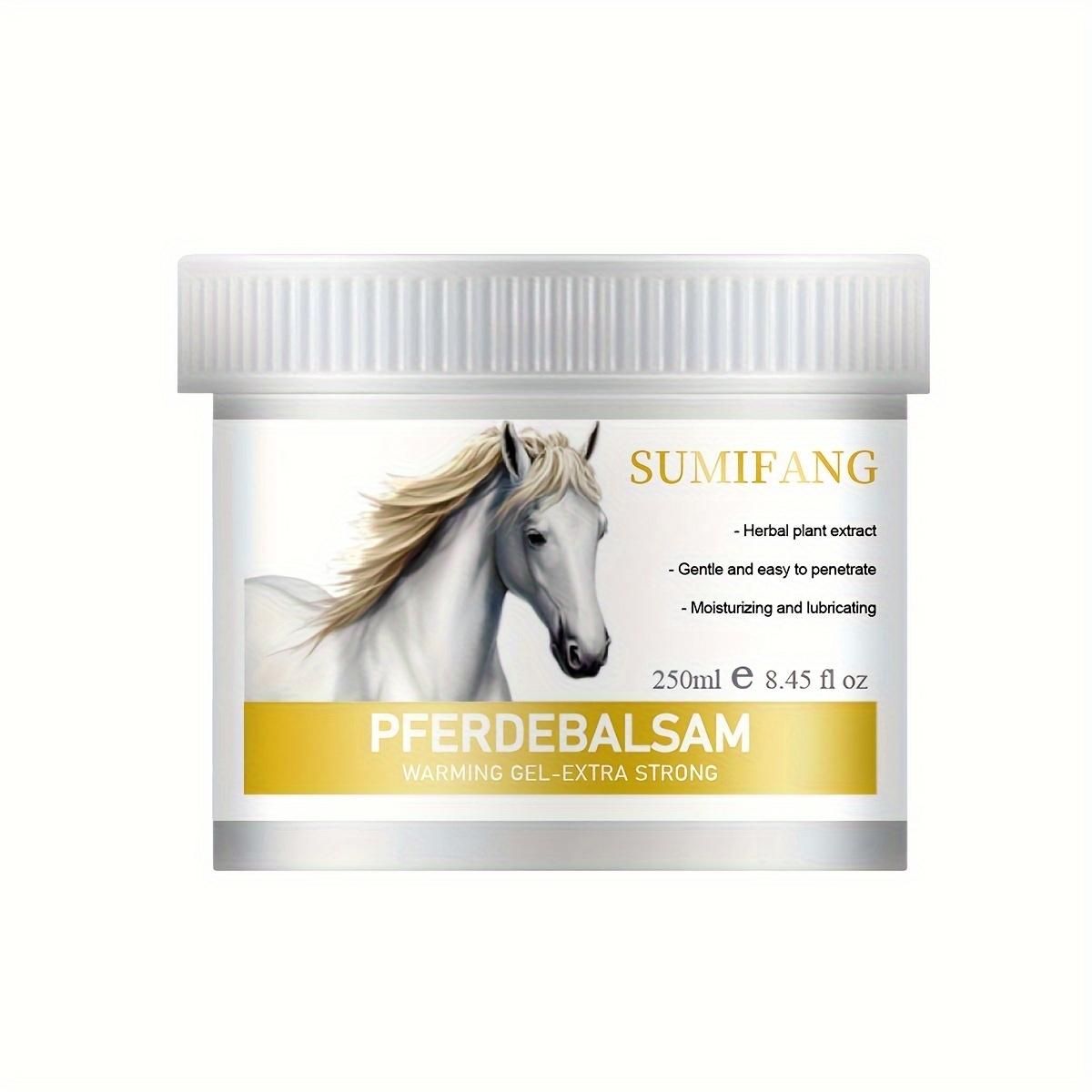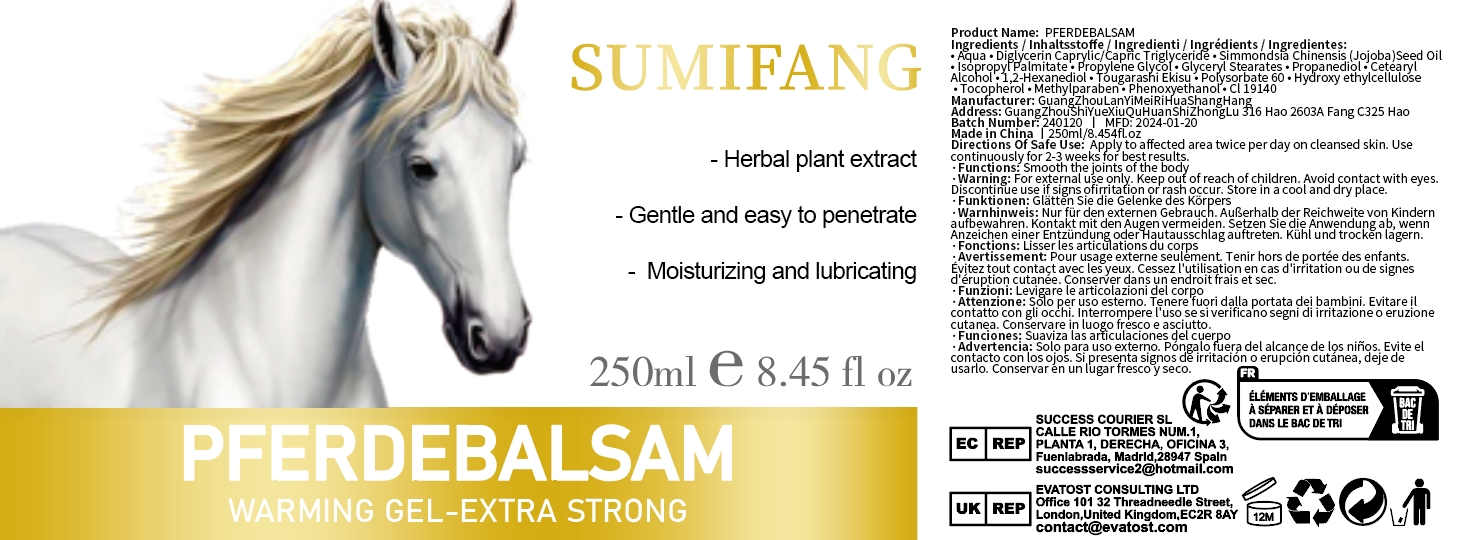 DRUG LABEL: PFERDEBALSAM
NDC: 84025-193 | Form: LOTION
Manufacturer: Guangzhou Yanxi Biotechnology Co.. Ltd
Category: otc | Type: HUMAN OTC DRUG LABEL
Date: 20240924

ACTIVE INGREDIENTS: 1,2-HEXANEDIOL 3 mg/250 mL; ISOPROPYL PALMITATE 5 mg/250 mL
INACTIVE INGREDIENTS: WATER

DOSAGE AND ADMINISTRATION

Body lotion for moisturizing care

INDICATIONS AND USAGE

For skin care

INACTIVE INGREDIENT

AQUA

WARNINGS

Keep out of children

keep out of children

PURPOSE

Effectively moisturizes the skin